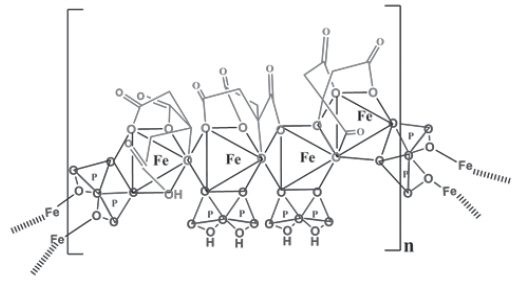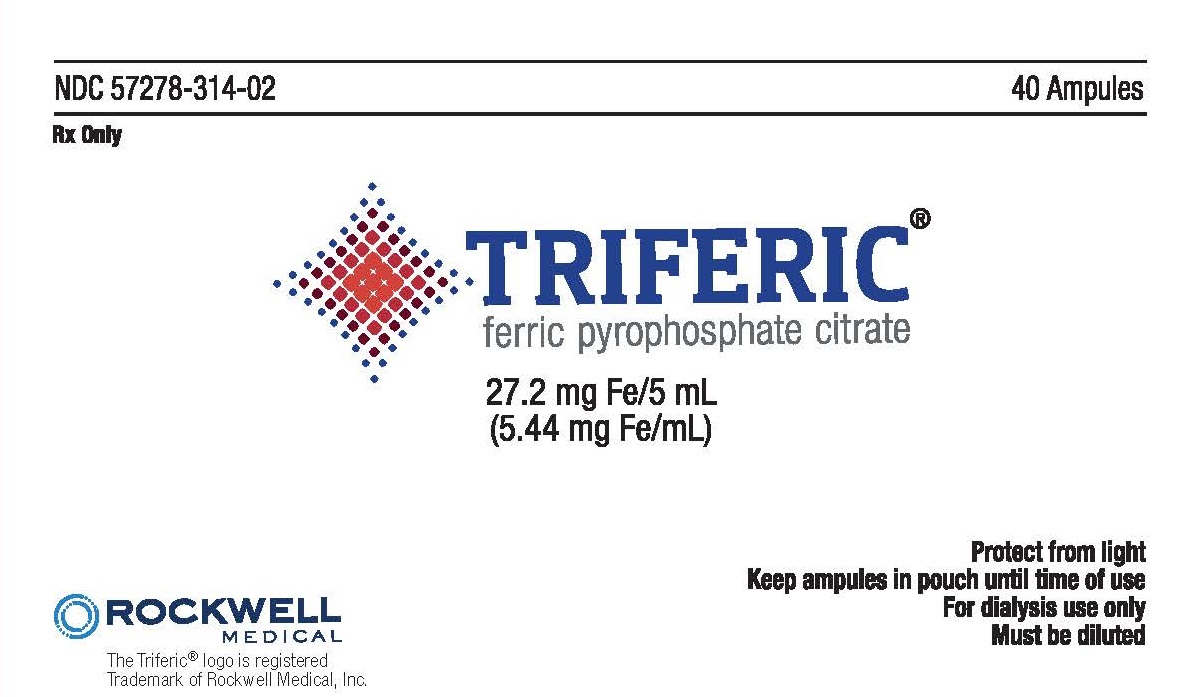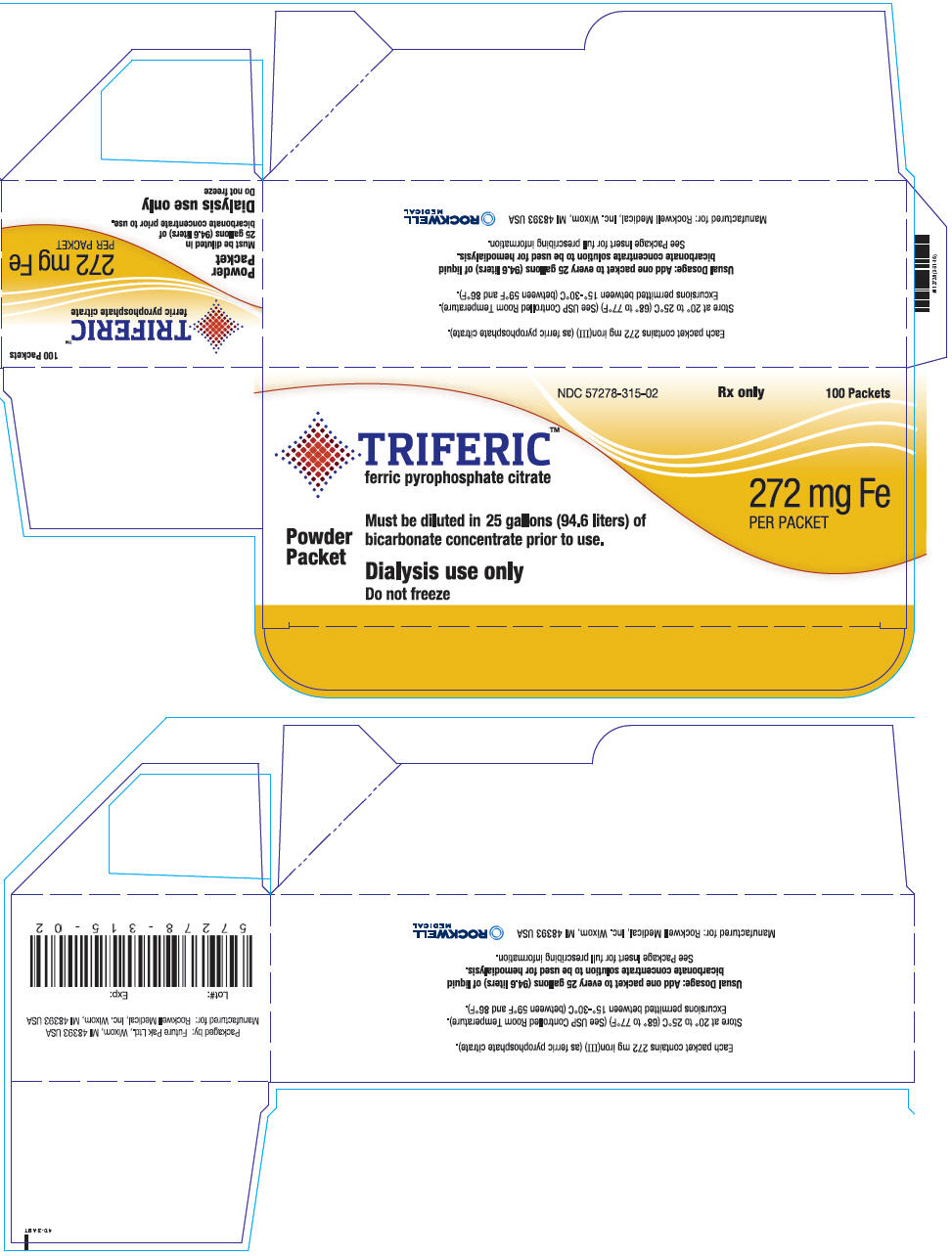 DRUG LABEL: Triferic
NDC: 57278-314 | Form: SOLUTION
Manufacturer: Rockwell Medical, Inc
Category: prescription | Type: HUMAN PRESCRIPTION DRUG LABEL
Date: 20200915

ACTIVE INGREDIENTS: FERRIC PYROPHOSPHATE CITRATE 5.44 mg/1 mL

HIGHLIGHTS OF PRESCRIBING INFORMATION

These highlights do not include all the information needed to use TRIFERIC safely and effectively. See full prescribing information for TRIFERIC.
TRIFERIC® (ferric pyrophosphate citrate) solution, for hemodialysis use
TRIFERIC® (ferric pyrophosphate citrate) for solution, for hemodialysis use
Initial U.S. Approval: 2015

1 INDICATIONS AND USAGE

TRIFERIC is an iron replacement product indicated for the replacement of iron to maintain hemoglobin in adult patients with hemodialysis-dependent chronic kidney disease (HDD-CKD). (1)

Limitation of Use

Triferic is not intended for use in patients receiving peritoneal dialysis. (1)

Triferic has not been studied in patients receiving home hemodialysis. (1)

2 DOSAGE AND ADMINISTRATION

- Add one 5 mL ampule of Triferic solution to each 2.5 gallons of bicarbonate concentrate to achieve a concentration of iron (III) in the final hemodialysate of 2 micromolar (110 mcg/L). (2.1)
- Add one packet of Triferic powder to each 25 gallons of bicarbonate concentrate to achieve a concentration of iron (III) in the final hemodialysate of 2 micromolar (110 mcg/L). (2.1)

3 DOSAGE FORMS AND STRENGTHS

27.2 mg of iron (III) per 5 mL ampule as Triferic solution (5.44 mg of iron (III) per mL). (3)

272 mg of iron (III) per packet as Triferic powder. (3)

4 CONTRAINDICATIONS

None

5 WARNINGS AND PRECAUTIONS

Hypersensitivity Reactions: Observe for signs and symptoms of hypersensitivity during and after hemodialysis and until clinically stable. (5.1)

6 ADVERSE REACTIONS

The most common adverse reactions (incidence >3%) are headache, peripheral edema, asthenia, AV fistula thrombosis, urinary tract infection, AV fistula site hemorrhage, pyrexia, fatigue, procedural hypotension, muscle spasms, pain in extremity, back pain, and dyspnea.

To report SUSPECTED ADVERSE REACTIONS, contact Rockwell Medical at 1-855-333-4315 or 1-248-960-9009 or FDA at 1-800-FDA-1088 or www.fda.gov/medwatch.

8 USE IN SPECIFIC POPULATIONS

Pregnancy: Based on animal data may cause fetal harm. (8.1)

See 17 for PATIENT COUNSELING INFORMATION

FULL PRESCRIBING INFORMATION

1 INDICATIONS AND USAGE

Triferic is an iron replacement product indicated for the replacement of iron to maintain hemoglobin in adult patients with hemodialysis-dependent chronic kidney disease (HDD-CKD).

1.1 Limitation of Use

Triferic is not intended for use in patients receiving peritoneal dialysis.

Triferic has not been studied in patients receiving home hemodialysis.

2 DOSAGE AND ADMINISTRATION

2.1 Recommended Dosage

Inspect Triferic solution in ampules for signs of precipitation prior to mixing with the bicarbonate concentrate. Triferic solution should appear slightly yellow-green in color.

Triferic solution or powder should only be added to the bicarbonate concentrate and should NOT be added to acid concentrate mixtures.

Add Triferic solution or powder to bicarbonate concentrate used for the generation of hemodialysate. The concentration of iron (III) in the final hemodialysate is 2 micromolar (110 mcg/L).

- Add one 5 mL ampule of Triferic solution to 2.5 gallons (9.46 liters) of bicarbonate concentrate. Multiple 5 mL ampules can be added to the master bicarbonate mix at each center at a ratio of one (1) ampule for each 2.5 gallons (9.46 liters) of bicarbonate concentrate.
- Add one packet of Triferic powder to 25 gallons (94.6 liters) of bicarbonate concentrate. Multiple packets can be added to the master bicarbonate mix and distribution system at each center at a ratio of one (1) 272 mg packet for each 25 gallons of bicarbonate concentrate.

Administer Triferic to patients at each dialysis procedure for as long as patients are receiving maintenance hemodialysis therapy for CKD.

Dosage of Triferic solution is expressed as mg of iron (III). Each mL of Triferic solution contains 5.44 mg of iron as iron(III).

Hemodialysis bicarbonate solutions should be used within 24 hours of the preparation of the bicarbonate concentrate mixture.

3 DOSAGE FORMS AND STRENGTHS

Injection: 27.2 mg iron(III) per 5 mL (5.44 mg iron(III) per mL) clear slightly yellow-green solution in single dose ampule.

For Injection: 272 mg iron(III) of ferric pyrophosphate citrate as slightly yellow-green powder Packet

4 CONTRAINDICATIONS

None

5 WARNINGS AND PRECAUTIONS

5.1 Hypersensitivity Reactions

Serious hypersensitivity reactions, including anaphylactic-type reactions, some of which have been life-threatening and fatal, have been reported in patients receiving parenteral iron products. Patients may present with shock, clinically significant hypotension, loss of consciousness, and/or collapse. Monitor patients for signs and symptoms of hypersensitivity during and after hemodialysis until clinically stable. Personnel and therapies should be immediately available for the treatment of serious hypersensitivity reactions [ see Adverse Reactions (6.1)].

Hypersensitivity reactions have been reported in 1 (0.3%) of 292 patients receiving Triferic in two randomized clinical trials.

5.2 Iron Laboratory Testing

Iron status should be determined on pre-dialysis blood samples. Post dialysis serum iron parameters may overestimate serum iron and transferrin saturation.

6 ADVERSE REACTIONS

The following adverse reactions are described below and elsewhere in the labeling:

- Hypersensitivity reactions [ see Warnings and Precautions (5.1)].

6.1 Clinical Trials Experience

Because clinical trials are conducted under widely varying conditions, adverse reaction rates observed in the clinical trials of a drug may not reflect the rates observed in practice.

In two randomized, placebo-controlled clinical trials, a total of 292 patients were administered Triferic for periods of up to 1 year [ see Clinical Studies (14)]. The mean total exposure in the randomized treatment period was 5 months. A total of 296 patients received placebo treatment for a similar time period. In the two studies, 64% were male and 54% were Caucasian. The median age of patients was 60 years (range, 20 to 89 years).

Adverse events occurring in 3% or greater of patients treated with Triferic in the randomized clinical trials are listed in Table 1.

Table 1: Adverse Reactions Reported in Two Clinical Trials in at Least 3% of Patients Receiving Triferic and at an Incidence at Least 1% Greater than Placebo
System Organ Class Preferred Term | Triferic N=292 n (%) | Placebo N=296 n (%)
Number of patients with at least one adverse reaction | 229 (78.4) | 223 (75.3)
General Disorders and Administration Site Conditions
Peripheral edema | 20 (6.8) | 11 (3.7)
Pyrexia | 13 (4.5) | 9 (3.0)
Asthenia | 12 (4.1) | 9 (3.0)
Fatigue | 11 (3.8) | 6 (2.0)
Infections and Infestations
Urinary tract infection | 13 (4.5) | 4 (1.4)
Injury, Poisoning, and Procedural Complications
Procedural hypotension | 63 (21.6) | 57 (19.3)
Arteriovenous fistula thrombosis | 10 (3.4) | 6 (2.0)
Arteriovenous fistula site hemorrhage | 10 (3.4) | 5 (1.7)
Musculoskeletal and Connective Tissue Disorders
Muscle spasms | 28 (9.6) | 24 (8.1)
Pain in extremity | 20 (6.8) | 17 (5.7)
Back pain | 13 (4.5) | 10 (3.4)
Nervous System Disorders
Headache | 27 (9.2) | 16 (5.4)
Respiratory, Thoracic and Mediastinal Disorders
Dyspnea | 17 (5.8) | 13 (4.4)

Adverse Reactions Leading to Treatment Discontinuation

In clinical trials, adverse reactions leading to treatment discontinuation included headache, asthenia, dizziness, constipation, nausea, hypersensitivity reactions, intradialytic hypotension, pruritus, and pyrexia.

Adverse reactions reported in the treatment extension period were similar to those observed in the randomized clinical studies.

8 USE IN SPECIFIC POPULATIONS

8.1 Pregnancy

Risk Summary

There are no data on Triferic use in pregnant women to inform a drug-associated risk of major birth defects and miscarriage. In pregnant rats and rabbits, ferric pyrophosphate citrate caused adverse developmental outcomes at maternally toxic dose levels that were higher than the maximum theoretical amount of iron transferred to patients from Triferic. Use Triferic during pregnancy only if the potential benefit justifies the potential risk to the fetus.

The estimated background risk of major birth defects and miscarriage for the indicated population is unknown. All pregnancies have a background of birth defect, loss, or other adverse outcomes. In the US. general population, the estimated background risk of major birth defects and miscarriage in clinically recognized pregnancies is 2-4% and 15-20% respectively.

Data

Animal Data

In a fertility and early embryonic development study in female rats, the maternally toxic ferric pyrophosphate citrate dose of 40 mg/kg administered three times per week by intravenous (IV) infusion was not toxic to the developing embryo.

In embryo-fetal developmental toxicity studies, ferric pyrophosphate citrate was administered during the period of organogenesis as a one-hour IV infusion to pregnant rats and rabbits. No maternal or developmental toxicity was observed at doses up to 30 mg/kg/day in rats and 20 mg/kg/day in rabbits. Maternally toxic doses affected embryo-fetal development, resulting in post-implantation loss due to early resorptions, abnormal placentae, decreased fetal body weight and fetal head and vertebral malformations at 90 mg/kg/day in rats and vertebral malformations at 40 mg/kg/day in rabbits.

A pre-and post-natal development study was conducted in pregnant rats with intravenous doses of ferric pyrophosphate citrate up to 90 mg/kg/day. The maternally toxic dose of 90 mg/kg/day resulted in reductions in the number of live offspring and lower offspring body weights. There were no adverse effects on survival of offspring at doses up to 30 mg/kg/day, or on behavior, sexual maturation or reproductive parameters of offspring at any dose level.

Data

Animal Data

In a fertility and early embryonic development study in female rats, the maternally toxic ferric pyrophosphate citrate dose of 40 mg/kg administered three times per week by intravenous (IV) infusion was not toxic to the developing embryo.

In embryo-fetal developmental toxicity studies, ferric pyrophosphate citrate was administered during the period of organogenesis as a one-hour IV infusion to pregnant rats and rabbits. No maternal or developmental toxicity was observed at doses up to 30 mg/kg/day in rats and 20 mg/kg/day in rabbits. Maternally toxic doses affected embryo-fetal development, resulting in post-implantation loss due to early resorptions, abnormal placentae, decreased fetal body weight and fetal head and vertebral malformations at 90 mg/kg/day in rats and vertebral malformations at 40 mg/kg/day in rabbits.

A pre-and post-natal development study was conducted in pregnant rats with intravenous doses of ferric pyrophosphate citrate up to 90 mg/kg/day. The maternally toxic dose of 90 mg/kg/day resulted in reductions in the number of live offspring and lower offspring body weights. There were no adverse effects on survival of offspring at doses up to 30 mg/kg/day, or on behavior, sexual maturation or reproductive parameters of offspring at any dose level.

8.2 Lactation

There is no information regarding the presence of Triferic in human milk, the effects on the breastfed child or the effect on milk production. The developmental and health benefits of breastfeeding should be considered along with the mother's clinical need for Triferic and any potential adverse effects on the breastfed child from Triferic or from the underlying maternal condition.

8.3 Females and Males of Reproductive Potential

Triferic may cause fetal harm when administered to pregnant women. Advise females of reproductive potential to use effective contraception measures to prevent pregnancy during treatment with Triferic and for at least 2 weeks following completion of therapy.

8.4 Pediatric Use

Safety and effectiveness have not been established in pediatric patients.

8.5 Geriatric Use

In controlled clinical trials, 99 (28.6%) patients ≥ 65 years of age were treated with Triferic. No overall differences in safety and efficacy were observed between older and younger patients in these trials [ see Clinical Studies (14)].

11 DESCRIPTION

Triferic (ferric pyrophosphate citrate) is a mixed-ligand iron complex in which iron (III) is bound to pyrophosphate and citrate. It has a molecular formula of Fe4(C6H4O7)3(H2P2O7)2(P2O7) and a relative molecular weight of approximately 1313 daltons. Triferic contains iron (7.5-9.0% w/w), citrate (15-22% w/w), pyrophosphate (15-22% w/w), phosphate (< 2% w/w), sodium (18-25% w/w) and sulfate (20-35%). Ferric pyrophosphate citrate has the following molecular structure:

Triferic solution:
Triferic (ferric pyrophosphate citrate) solution–is a clear, slightly yellow-green color sterile solution containing 27.2 mg of elemental iron (III) per 5 mL (5.44 mg iron (III) per mL) filled in a 5 mL low density polyethylene (LDPE) ampule. Each Triferic ampule contains iron (7.5-9.0% w/w), citrate (15-22% w/w), pyrophosphate (15-22% w/w), phosphate (< 2% w/w), sodium (18‑25% w/w) and sulfate (20-35%). One Triferic 5 mL ampule is added to 2.5 gallons (9.46 L) of bicarbonate concentrate.
Triferic powder Packets:
Triferic (ferric pyrophosphate citrate) powder is a slightly yellow-green powder, packaged in single use paper, polyethylene and aluminum foil packets, each containing 272.0 mg of elemental iron (III). Each Triferic packet contains iron (7.5-9.0% w/w), citrate (15-22% w/w), pyrophosphate (15-22% w/w), phosphate (< 2% w/w), sodium (18‑25% w/w) and sulfate (20-35%). One Triferic powder packet is added to 25 (94.6 L) gallons of master bicarbonate mix.

12 CLINICAL PHARMACOLOGY

12.1 Mechanism of Action

Triferic contains iron in the form of ferric pyrophosphate citrate and is added to hemodialysate solution to be administered to patients by transfer across the dialyzer membrane. Iron delivered into the circulation binds to transferrin for transport to erythroid precursor cells to be incorporated into hemoglobin.

12.3 Pharmacokinetics

The pharmacokinetics of serum iron was investigated in healthy volunteers administered 2.5, 5, 7.5 and 10 mg Triferic intravenously over 4 hours, or 15 mg and 20 mg Triferic intravenously over 12 hours. After correcting for the basal iron levels, the AUC and Cmax of baseline-corrected serum iron increased in a dose-proportional manner. The half-life of serum iron was approximately 1.48 hours, the mean clearance (CL) ranged from 0.406 to 0.556 L/hour, the mean apparent volume of distribution (Vz) ranged from 0.765 to 0.859 L after a 4-hour intravenous administration of Triferic. Compared to the 4-hour infusion of Triferic, higher mean CL and Vz were observed following the administration of Triferic 15 mg (CL = 0.672 L/hour and Vz = 1.66 L) and Triferic 20 mg (CL = 0.661 L/hour, Vz = 2.08L) infused over 12 hours. In a study that assessed the impact of different dialysis conditions on iron delivery in patients administered Triferic via hemodialysis, a reduction of the blood and dialysate flow rates (Qb/Qd of 200/400 mL/min vs. ≥ 350/ ≥ 600 mL/min) resulted in a 33% decrease in the median cumulative iron delivered.

13 NONCLINICAL TOXICOLOGY

13.1 Carcinogenesis, Mutagenesis, Impairment of Fertility

Studies examining the carcinogenic potential of ferric pyrophosphate citrate have not been conducted.

Ferric pyrophosphate citrate was clastogenic in the in vitro chromosomal aberration assay in CHO cells in the presence of metabolic activation. Ferric pyrophosphate citrate was not mutagenic in the in vitro bacterial reverse mutation (Ames) test or clastogenic in the in vitro chromosomal aberration assay in CHO cells in the absence of metabolic activation or in the in vivo mouse micronucleus assay.

In a combined male and female fertility study in rats, ferric pyrophosphate citrate was administered intravenously over one hour three times per week at doses of up to 40 mg/kg. No adverse effects on fertility or reproduction were noted.

14 CLINICAL STUDIES

The safety and efficacy of Triferic in patients with HDD-CKD was assessed in two randomized, single blind, placebo-controlled clinical trials. Patients with hemoglobin of 9 g/dL to 12 g/dL with TSAT > 20% and serum ferritin concentrations > 200 mcg/L were enrolled. Patients were to remain in randomized treatment until pre-specified hemoglobin or ferritin criteria were met, indicating the need for a change in anemia management, or if they completed 48 weeks. Triferic was added to the bicarbonate concentrate with a final concentration of 110 mcg iron/L in the dialysate and was administered 3 or 4 times per week during hemodialysis. Most patients were receiving a stable dose of erythropoiesis stimulating agents (ESAs) at baseline. After randomization, patients' ESA doses were not to be changed.

In Study 1, the mean age of patients was 58 years (range 23 to 89); 32% were female, 55% were Caucasian, 32% were African American, and 13% were other races.

In Study 2, the mean age of patients was 58 years (range 20 to 89); 41% were female, 54% were Caucasian, 40% were African American, and 6% were other races.

The primary endpoint of the studies was the mean change in hemoglobin from baseline to the end-of-treatment period (average hemoglobin of the last one-sixth (1/6th) of the time in the randomized treatment period). About 18% of patients completed the planned 48-week treatment duration.

Table 2 shows the mean changes in hemoglobin (Hgb) and iron parameters in each treatment group from baseline to the end-of-treatment period for the ITT population.

Table 2: Changes from Baseline to End-of-Treatment in Hemoglobin, Ferritin, Reticulocyte Hgb (CHr), and Transferrin Saturation (TSAT)
 | Study 1 |  | Study 2
 | Triferic n=152 | Placebo n=153 | Triferic n=147 | Placebo n=147
Baseline Hemoglobin Mean ± (SD), g/dL | 10.96 (0.592) | 10.91 (0.632) | 10.96 (0.605) | 10.94 (0.622)
Hemoglobin, Change from Baseline to End-of-Treatment Mean ± (SD), g/dL | -0.03 (1.147) [p < 0.05 for primary efficacy endpoint] | -0.38 (1.240) | -0.08 (1.152) | -0.44 (1.157)
Baseline Ferritin Mean (SD), mcg/L | 508.2 (193.55) | 509.3 (209.06) | 519.0 (201.56) | 478.4 (200.59)
Ferritin, Change from Baseline to End-of-Treatment Mean (SD), mcg/L | -70.8 (132.41) | -141.2 (187.74) | -65.3 (162.45) | -120.9 (268.19)
Baseline Reticulocyte Hemoglobin (CHr) Mean (SD), pg | 32.37 (1.967) | 32.53 (1.965) | 32.56 (2.210) | 32.57 (1.932)
CHr, Change from Baseline to End-of-Treatment Mean (SD), pg | -0.22 (1.191) | -0.90 (1.407) | -0.55 (1.441) | -0.85 (1.474)
Baseline TSAT Mean (SD), % | 28.2 (8.23) | 27.1 (7.76) | 28.0 (8.15) | 28.2 (8.52)
TSAT, Change from Baseline to End-of-Treatment) Mean (SD), % | -1.0 (9.07) | -2.9 (7.65) | -0.9 (7.54) | -3.6 (7.29)

16 HOW SUPPLIED/STORAGE AND HANDLING

16.1 How Supplied

Triferic is available in ampules or packets in the following package sizes:

NDC Code | Package Description | Amount/Total Volume in Ampule
 | 5 mL Ampule | 27.2 mg iron (III)/ 5mL as Triferic solution (5.44 mg of iron (III) per mL)
NDC 57278-314-01 | 5 X 5 mL Ampules per Pouch | 27.2 mg iron (III)/ 5mL as Triferic solution (5.44 mg of iron (III) per mL)
NDC 57278-314-02 | 8 Pouches per Carton | 27.2 mg iron (III)/ 5mL as Triferic solution (5.44 mg of iron (III) per mL)

NDC Code | Package Description | Amount/Packet
NDC 57278-315-01 | Packet | 272 mg iron (III)/ packet as Triferic powder
NDC 57278-315-02 | 100 Packets per Carton | 272 mg iron (III)/ packet as Triferic powder

16.2 Storage

Store ampules protected from light in the aluminum pouch at controlled room temperature (20° to 25°C [68° to 77°F]); excursions permitted to 15°to 30°C (59° to 86°F) [See USP Controlled Room Temperature].

Store packets at controlled room temperature (20° to 25°C [68° to 77°F]); excursions permitted to 15° to 30°C (59° to 86°F) [See USP Controlled Room Temperature].

17 PATIENT COUNSELING INFORMATION

Prior to the administration of Triferic:

- Question patients regarding any prior history of reactions to parenteral iron products.
- Advise patients of the risks associated with Triferic.
- Advise patient to report any signs and symptoms of hypersensitivity that may develop during and after the dialysis session, such as rash, itching, dizziness, lightheadedness, swelling and breathing problems [ see Warnings and Precautions (5)].
- Advise females of reproductive potential to use effective contraception measures to prevent pregnancy during treatment with Triferic and for at least 2 weeks following completion of therapy

Manufactured for: Rockwell Medical, Inc., Wixom, MI 48393

PRINCIPAL DISPLAY PANEL - 40 Ampule Carton

NDC 57278-314-02
40 Ampules

Rx Only

TRIFERIC™
ferric pyrophosphate citrate

27.2 mg Fe/5 mL
(5.44 mg Fe/mL)

ROCKWELL
MEDICAL

Protect from light
Keep ampules in pouch until time of use
For dialysis use only
Must be diluted

PRINCIPAL DISPLAY PANEL - 100 Packet Carton

NDC 57278-315-02
Rx only
100 Packets

TRIFERIC™
ferric pyrophosphate citrate

Powder
Packet

Must be diluted in 25 gallons (94.6 liters) of
bicarbonate concentrate prior to use.

Dialysis use only
Do not freeze

272 mg Fe
PER PACKET